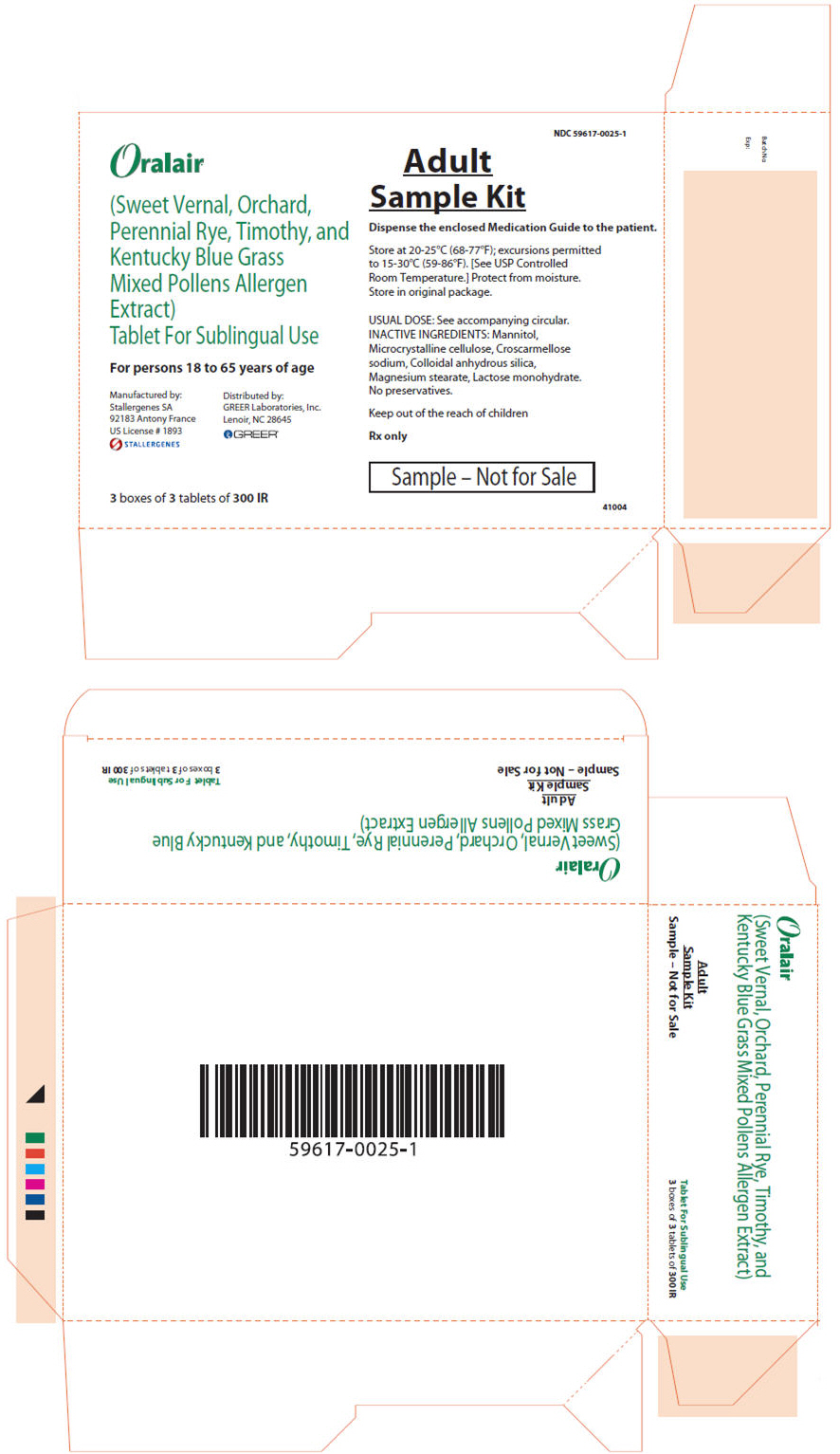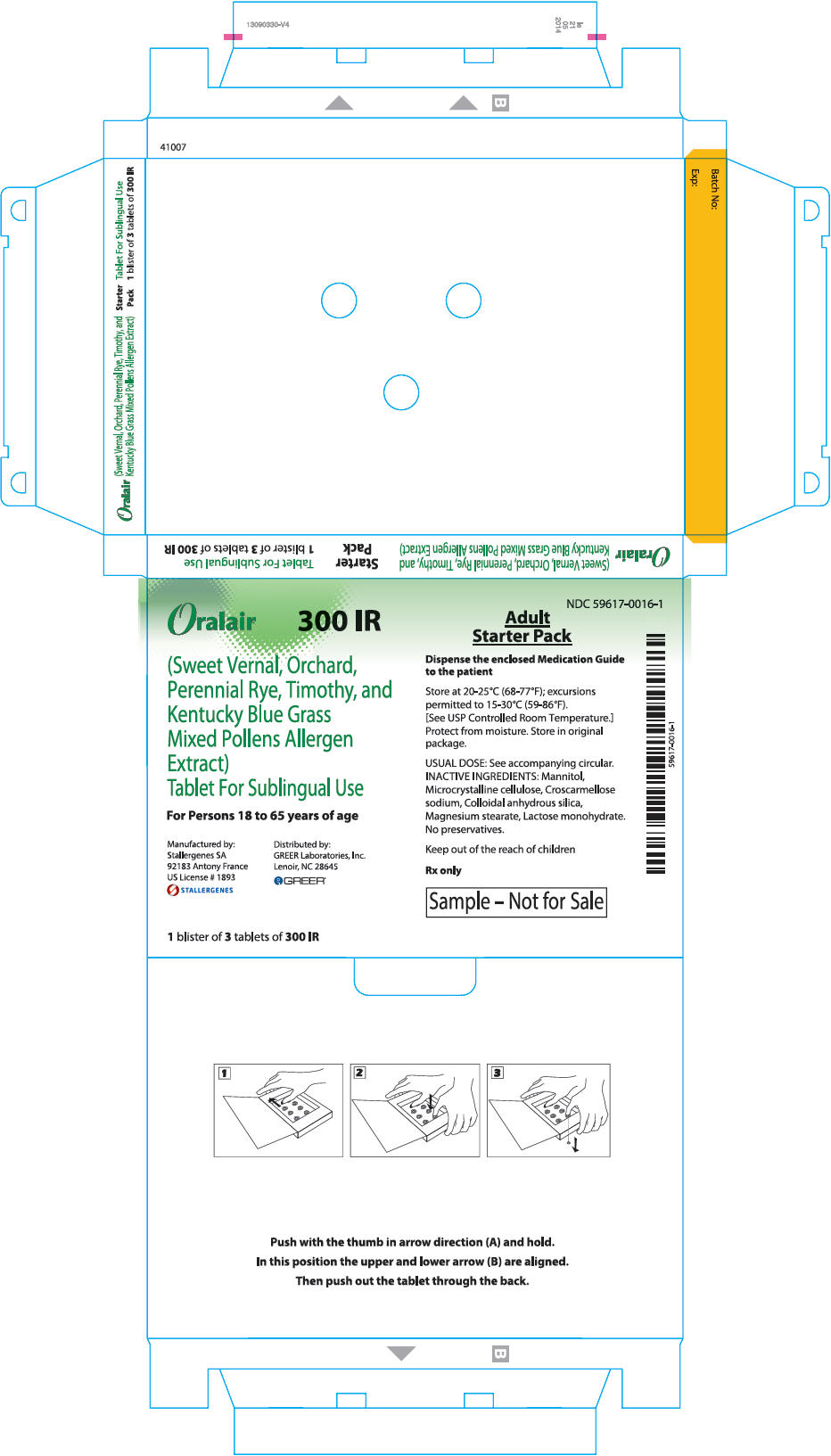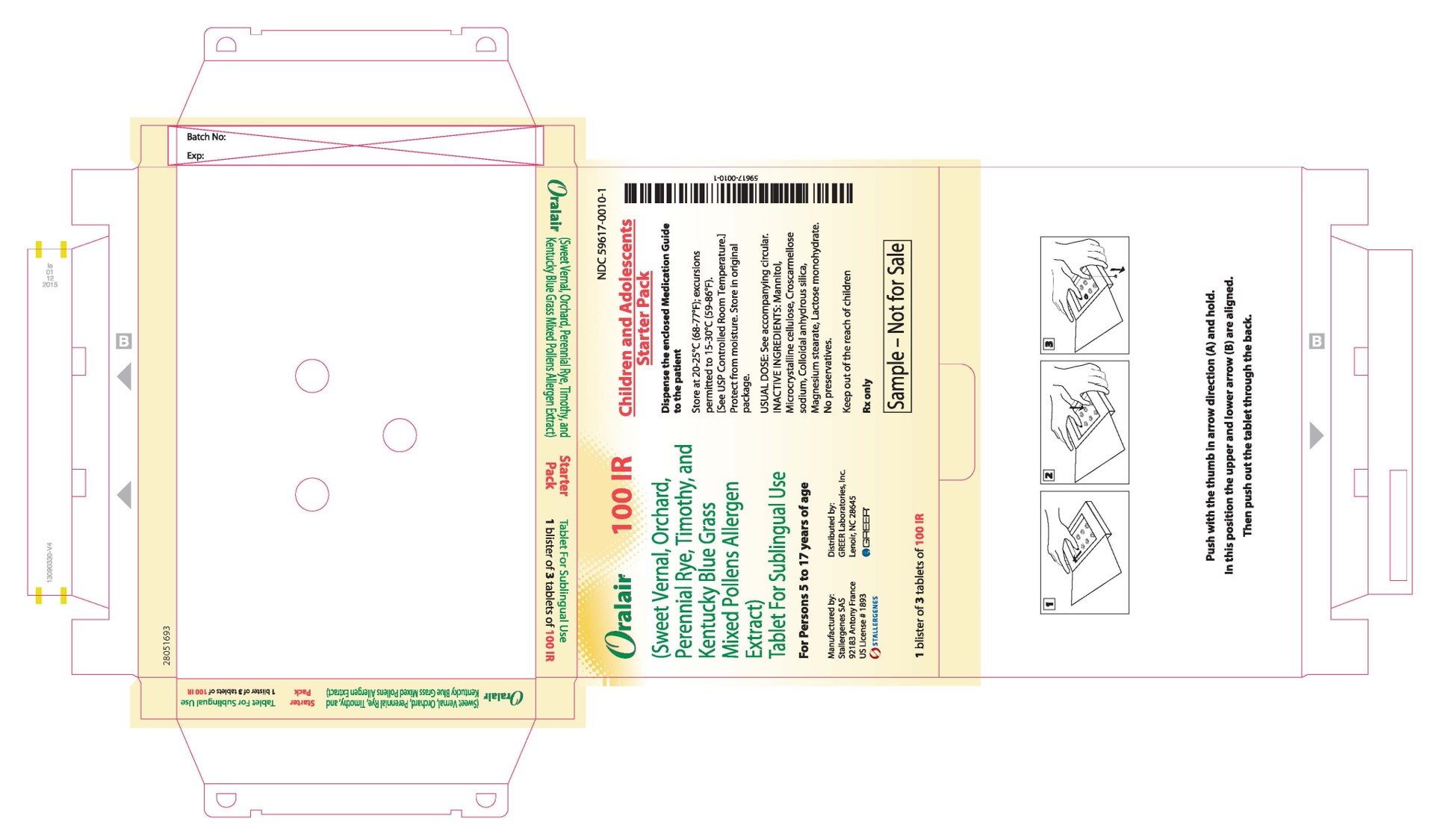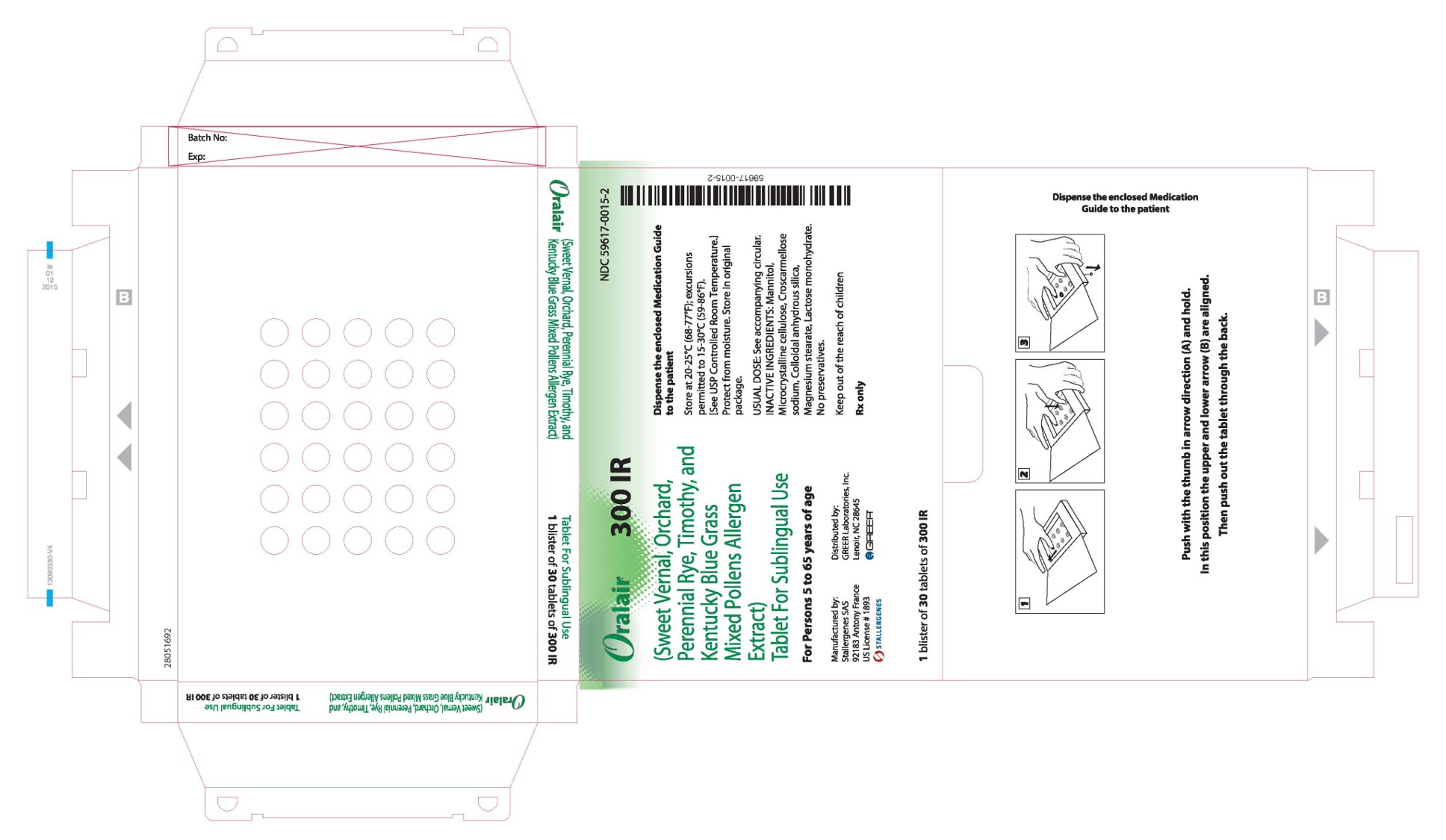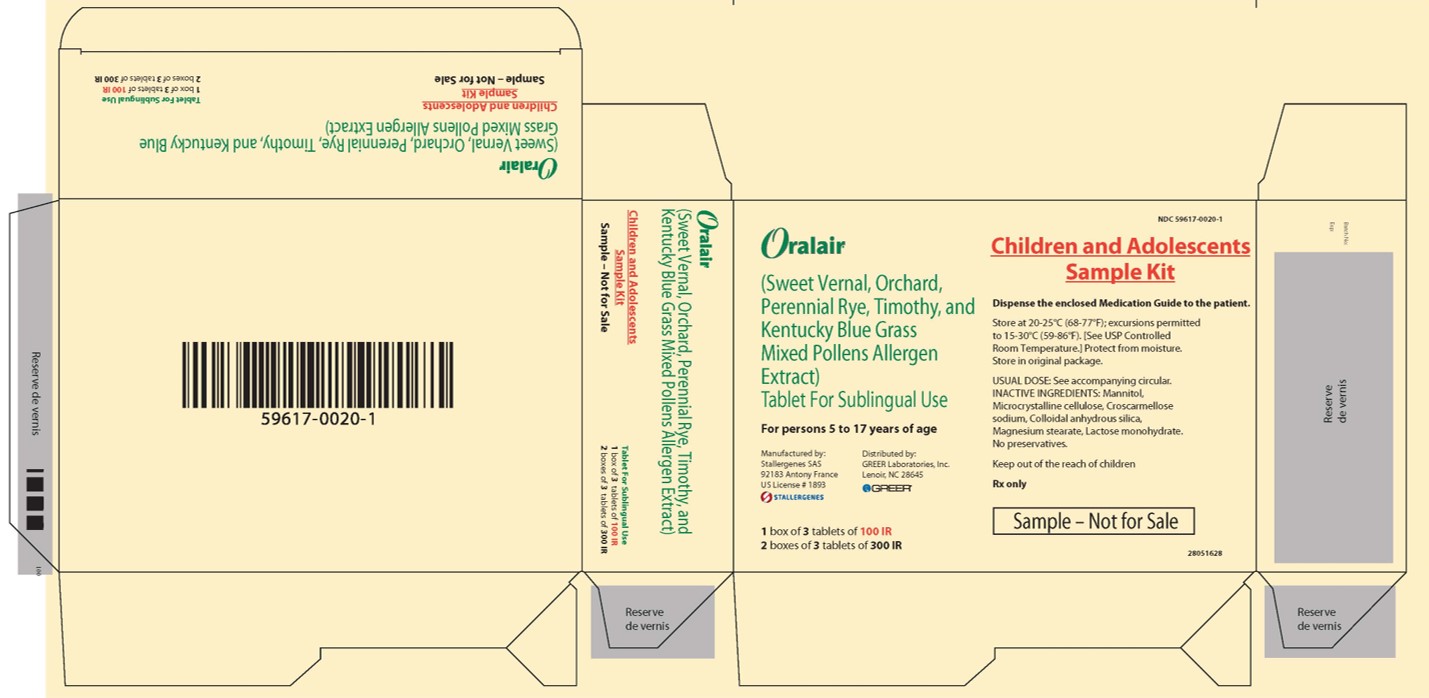 DRUG LABEL: Oralair
NDC: 59617-0025 | Form: KIT | Route: SUBLINGUAL
Manufacturer: Stallergenes
Category: other | Type: STANDARDIZED ALLERGENIC
Date: 20250609

ACTIVE INGREDIENTS: PHLEUM PRATENSE POLLEN 300 [IR]/1 1; ANTHOXANTHUM ODORATUM POLLEN 300 [IR]/1 1; DACTYLIS GLOMERATA POLLEN 300 [IR]/1 1; POA PRATENSIS POLLEN 300 [IR]/1 1; LOLIUM PERENNE POLLEN 300 [IR]/1 1; PHLEUM PRATENSE POLLEN 300 [IR]/1 1; ANTHOXANTHUM ODORATUM POLLEN 300 [IR]/1 1; DACTYLIS GLOMERATA POLLEN 300 [IR]/1 1; POA PRATENSIS POLLEN 300 [IR]/1 1; LOLIUM PERENNE POLLEN 300 [IR]/1 1
INACTIVE INGREDIENTS: SILICON DIOXIDE; LACTOSE MONOHYDRATE; CROSCARMELLOSE SODIUM; MAGNESIUM STEARATE; SILICON DIOXIDE; LACTOSE MONOHYDRATE; CROSCARMELLOSE SODIUM; MAGNESIUM STEARATE

These highlights do not include all the information needed to use ORALAIR safely and effectively. See full prescribing information for ORALAIR.
ORALAIR® (Sweet Vernal, Orchard, Perennial Rye, Timothy, and Kentucky Blue Grass Mixed Pollens Allergen Extract)
Tablet for Sublingual Use
Initial U.S. Approval: 2014

HIGHLIGHTS OF PRESCRIBING INFORMATION

These highlights do not include all the information needed to use ORALAIR safely and effectively. See full prescribing information for ORALAIR.

ORALAIR® (Sweet Vernal, Orchard, Perennial Rye, Timothy, and Kentucky Blue Grass Mixed Pollens Allergen Extract)

Tablet for Sublingual Use

Initial U.S. Approval: 2014

WARNING: SEVERE ALLERGIC REACTIONS
See full prescribing information for complete boxed warning

- ORALAIR can cause life-threatening allergic reactions such as anaphylaxis and severe laryngopharyngeal edema. (5.1)
- Do not administer ORALAIR to patients with severe, unstable or uncontrolled asthma. (4)
- Observe patients in the office for at least 30 minutes following the initial dose. (5.1)
- Prescribe auto-injectable epinephrine, instruct and train patients on its appropriate use, and instruct patients to seek immediate medical care upon its use. (5.2)
- ORALAIR may not be suitable for patients with certain underlying medical conditions that may reduce their ability to survive a serious allergic reaction. (5.2)
- ORALAIR may not be suitable for patients who may be unresponsive to epinephrine or inhaled bronchodilators, such as those taking beta-blockers. (5.2)

RECENT MAJOR CHANGES

Indications and Usage (1) | 11/2018
Dosage and Administration (2.1) | 11/2018

INDICATIONS AND USAGE

ORALAIR is an allergen extract indicated as immunotherapy for the treatment of grass pollen-induced allergic rhinitis with or without conjunctivitis confirmed by positive skin test or in vitro testing for pollen-specific IgE antibodies for any of the five grass species contained in this product. ORALAIR is approved for use in persons 5 through 65 years of age.

DOSAGE AND ADMINISTRATION

For sublingual use only.

Age (years) | Dose
Age (years) | Day 1 | Day 2 | Day 3 and following
5-17 | 100 IR | 2× 100 IR | 300 IR
18-65 | 300 IR | 300 IR | 300 IR

- Initiate treatment 4 months before the expected onset of each grass pollen season and continue treatment throughout the season. (2.2)
- Place the tablet under the tongue for at least 1 minute, until complete dissolution and then swallow. (2.2)
- Administer the first dose of ORALAIR under the supervision of a physician with experience in the diagnosis and treatment of severe allergic reactions. Observe the patient for at least 30 minutes. (2.1)

DOSAGE FORMS AND STRENGTHS

- Tablets, 100 IR and 300 IR (3)

CONTRAINDICATIONS

- Severe, unstable or uncontrolled asthma (4)
- History of any severe systemic allergic reaction or any severe local reaction to sublingual allergen immunotherapy (4)
- A history of eosinophilic esophagitis (4)
- Hypersensitivity to any of the inactive ingredients contained in this product (4)

WARNINGS AND PRECAUTIONS

- Inform patients of the signs and symptoms of severe allergic reactions and instruct them to seek immediate medical care and discontinue therapy should any of these occur. (5.1)
- In case of oral inflammation or wounds, stop treatment with ORALAIR to allow complete healing of the oral cavity. (5.5)

ADVERSE REACTIONS

Adverse reactions reported in > 5% of patients were: oral pruritus, throat irritation, ear pruritus, mouth edema, tongue pruritus, cough, asthma, oropharyngeal pain, tonsillitis, and oral paresthesia (6)

To report SUSPECTED ADVERSE REACTIONS, contact Stallergenes at 1-855-274-1322 or FDA at 1-800-FDA-1088 or www.fda.gov/medwatch

See 17 for Patient Counseling Information and FDA approved Medication Guide

WARNING: SEVERE ALLERGIC REACTIONS

- ORALAIR can cause life-threatening allergic reactions such as anaphylaxis and severe laryngopharyngeal restriction. (5.1)
- Do not administer ORALAIR to patients with severe, unstable or uncontrolled asthma. (4)
- Observe patients in the office for at least 30 minutes following the initial dose. (5.1)
- Prescribe auto-injectable epinephrine, instruct and train patients on its appropriate use, and instruct patients to seek immediate medical care upon its use. (5.2)
- ORALAIR may not be suitable for patients with certain underlying medical conditions that may reduce their ability to survive a serious allergic reaction. (5.2)
- ORALAIR may not be suitable for patients who may be unresponsive to epinephrine or inhaled bronchodilators, such as those taking beta-blockers. (5.2)

1 INDICATIONS AND USAGE

ORALAIR is an allergen extract indicated as immunotherapy for the treatment of grass pollen-induced allergic rhinitis with or without conjunctivitis confirmed by positive skin test or in vitro testing for pollen-specific IgE antibodies for any of the five grass species contained in this product. ORALAIR is approved for use in persons 5 through 65 years of age.

ORALAIR is not indicated for the immediate relief of allergy symptoms.

2 DOSAGE AND ADMINISTRATION

For sublingual use only.

2.1 Dose

For adults 18 through 65 years of age, the dose is 300 IR (index of reactivity) daily. For children and adolescents 5 through 17 years of age, the dose is increased over the first three days as shown in Table 1.

Table 1. Dosage for Adults and Children for the Days 1-3 (and following)
Age (years) | Dose
Age (years) | Day 1 | Day 2 | Day 3 and following
5-17 | 100 IR | 2x100 IR | 300 IR
18-65 | 300 IR | 300 IR | 300 IR

2.2 Administration

Administer the first dose of ORALAIR in a healthcare setting in which acute allergic reactions can be treated under the supervision of a physician with experience in the diagnosis and treatment of severe allergic reactions. After receiving the first dose of ORALAIR, observe the patient for at least 30 minutes to monitor for signs or symptoms of a severe systemic or a severe local allergic reaction. If the patient tolerates the first dose, the patient may take subsequent doses at home.

Administer ORALAIR to children under adult supervision.

Remove the ORALAIR tablet from the blister just prior to dosing.

Place the ORALAIR tablet immediately under the tongue until complete dissolution for at least 1 minute before swallowing.

Wash hands after handling the ORALAIR tablet.

Do not take the ORALAIR tablet with food or beverage. To avoid swallowing allergen extract, food or beverage should not be taken for 5 minutes following dissolution of the tablet.

Initiate treatment 4 months before the expected onset of each grass pollen season and maintain it throughout the grass pollen season.

Data regarding the safety of starting treatment during the pollen season are not available. Data regarding the safety of restarting treatment after missing a dose of ORALAIR are not available.

It is recommended that auto-injectable epinephrine be made available to patients prescribed ORALAIR. Patients who are prescribed epinephrine while receiving immunotherapy should be instructed in the proper use of emergency self-injection of epinephrine [ See Warnings and Precautions (5.2)].

3 DOSAGE FORMS AND STRENGTHS

ORALAIR tablets are available as follows:

- ORALAIR 100 IR tablets are round and biconvex, slightly speckled white to beige with "100" engraved on both sides
- ORALAIR 300 IR tablets are round and biconvex, slightly speckled white to beige with "300" engraved on both sides

4 CONTRAINDICATIONS

ORALAIR is contraindicated in patients with:

- Severe, unstable or uncontrolled asthma
- History of any severe systemic allergic reaction
- History of any severe local reaction to sublingual allergen immunotherapy
- A history of eosinophilic esophagitis
- Hypersensitivity to any of the inactive ingredients (mannitol, microcrystalline cellulose, croscarmellose sodium, colloidal anhydrous silica, magnesium stearate and lactose monohydrate) contained in this product [ See Description (11)]

5 WARNINGS AND PRECAUTIONS

5.1 Severe Allergic Reactions

ORALAIR can cause systemic allergic reactions including anaphylaxis which may be life-threatening. In addition, ORALAIR can cause severe local reactions, including laryngopharyngeal swelling, which can compromise breathing and be life-threatening.

Patients who have a systemic allergic reaction to ORALAIR should stop taking ORALAIR.

Patients who have either escalating or persistent local reactions to ORALAIR should be reevaluated and considered for discontinuation of ORALAIR.

Administer the initial dose of ORALAIR in a healthcare setting under the supervision of a physician prepared to manage a severe

systemic or a severe local allergic reaction. Observe patients in the office for at least 30 minutes following the initial dose of ORALAIR.

Severe and serious allergic reactions may require treatment with epinephrine [ See Warnings and Precautions (5.2)].

5.2 Epinephrine

Prescribe auto-injectable epinephrine to patients receiving ORALAIR. Instruct patients to recognize the signs and symptoms of a severe allergic reaction and in the proper use of emergency self-injection of epinephrine, and instruct patients to seek immediate medical care upon its use [ See Patient Counseling Information (17)].

ORALAIR may not be suitable for patients with certain medical conditions that may reduce the ability to survive a serious allergic reaction or increase the risk of adverse reactions after epinephrine administration. Examples of these medical conditions include but are not limited to: markedly compromised lung function (either chronic or acute), unstable angina, recent myocardial infarction, significant arrhythmia, and uncontrolled hypertension.

ORALAIR may not be suitable for patients who are taking medications that can potentiate or inhibit the effect of epinephrine. These medications include:

Βeta-adrenergic blockers: Patients taking beta-adrenergic blockers may be unresponsive to the usual doses of epinephrine used to treat serious systemic reactions, including anaphylaxis. Specifically, beta-adrenergic blockers antagonize the cardiostimulating and bronchodilating effects of epinephrine.

Alpha-adrenergic blockers, ergot alkaloids: Patients taking alpha-adrenergic blockers may be unresponsive to the usual doses of epinephrine used to treat serious systemic reactions, including anaphylaxis. Specifically, alpha-adrenergic blockers antagonize the vasoconstricting and hypertensive effects of epinephrine. Similarly, ergot alkaloids may reverse the pressor effects of epinephrine.

Tricyclic antidepressants, levothyroxine sodium, monoamine oxidase inhibitors and certain antihistamines: The adverse effects of epinephrine may be potentiated in patients taking tricyclic antidepressants, levothyroxine sodium, monoamine oxidase inhibitors, and the antihistamines chlorpheniramine, and diphenhydramine.

Cardiac glycosides, diuretics: Patients who receive epinephrine while taking cardiac glycosides or diuretics should be observed carefully for the development of cardiac arrhythmias.

5.3 Eosinophilic Esophagitis

Eosinophilic esophagitis has been reported in association with sublingual tablet immunotherapy [ See Contraindications (4) and Adverse Reactions (6.2)]. Discontinue ORALAIR and consider a diagnosis of eosinophilic esophagitis in patients who experience severe or persistent gastro-esophageal symptoms including dysphagia or chest pain.

5.4 Asthma

ORALAIR has not been studied in subjects with moderate or severe asthma or any subjects who required daily medication.

Immunotherapy with ORALAIR should be withheld if the patient is experiencing an acute asthma exacerbation. Reevaluate patients who have recurrent asthma exacerbations and consider discontinuation of ORALAIR.

5.5 Concomitant Allergen Immunotherapy

ORALAIR has not been studied in subjects receiving concomitant allergen immunotherapy. Concomitant dosing with other allergen immunotherapy may increase the likelihood of local or systemic adverse reactions to either subcutaneous or sublingual allergen immunotherapy.

5.6 Oral Inflammation

Stop treatment with ORALAIR to allow complete healing of the oral cavity in patients with oral inflammation (e.g., oral lichen planus, mouth ulcers or thrush) or oral wounds, such as those following oral surgery or dental extraction.

5.7 Initiation of ORALAIR Therapy during Grass Pollen Season

The risk of ORALAIR may be increased when treatment is initiated during the grass pollen season.

6 ADVERSE REACTIONS

Adverse reactions reported in > 5% of patients were: oral pruritus, throat irritation, ear pruritus, mouth edema, tongue pruritus, cough, oropharyngeal pain.

6.1 Clinical Trials Experience

Because clinical trials are conducted under widely varying conditions, adverse reaction rates observed in the clinical trials of a drug cannot be directly compared to rates in the clinical trials of another drug and may not reflect the rate observed in practice.

Adults

Overall, in 6 placebo-controlled clinical trials, 1,038 adults 18 through 65 years of age received at least one dose of ORALAIR 300IR, of whom 611 (59%) completed at least four months of therapy. Of study participants, 56% were male, 17% had a history of mild intermittent asthma at study entry, and 64% were polysensitized. Data on race and ethnicity were not systematically captured in the five European studies (N=805). In the US study (N=233), a limited number of patients reported their race as other than White/Caucasian (Black/African American: 5.6%, Asian: 2.6%, Other: 2.1%) or their ethnicity as Hispanic or Latino (3.0%). Adverse events were captured on a daily diary card that did not solicit for specific adverse events.

Across the six clinical studies, adverse reactions reported at an incidence of > 2% of ORALAIR recipients and at a greater incidence than that in participants treated with placebo are listed in Table 2.

Table 2. Adverse Reactions Reported by ≥2% of Adults Receiving ORALAIR 300 IR and at a Greater Incidence than that in Participants Treated with Placebo
Adverse Reactions | ORALAIR 300 IR (N=1,038) | PLACEBO (N=840)
Ear and labyrinth disorders
Ear pruritus | 8.4% | 0.6%
Respiratory, thoracic and mediastinal disorders
Throat irritation | 22.0% | 3.7%
Cough | 7.3% | 5.9%
Oropharyngeal pain | 5.1% | 3.7%
Pharyngeal edema | 3.8% | 0.1%
Gastrointestinal disorders
Oral pruritus | 25.1% | 5.0%
Edema mouth | 8.2% | 0.6%
Tongue pruritus | 7.9% | 0.7%
Lip edema | 4.4% | 0.4%
Paraesthesia oral | 4.3% | 1.0%
Abdominal pain | 4.2% | 1.3%
Dyspepsia | 3.9% | 0.4%
Tongue edema | 2.7% | 0.1%
Hypoaesthesia oral | 2.2% | 0.1%
Stomatitis | 2.1% | 0.7%
Skin and subcutaneous tissue disorders
Urticaria | 2.3% | 1.5%

Additional adverse reactions of interest that occurred in < 2% of ORALAIR recipients include dysphagia, nausea, vomiting, esophageal pain, gastritis, and gastroesophageal reflux.

Children and Adolescents

Overall, in placebo-controlled clinical trials, 154 children and adolescents 5 through 17 years of age received ORALAIR 300 IR, of whom 147 were exposed for more than 3 months. Of study participants, 66% were male, and 21% had a history of mild intermittent asthma at study entry. Data on race and ethnicity were not systematically captured.

The safety profile in the pediatric population, was generally similar to that of adults. In pediatric patients receiving ORALAIR, additional adverse reactions reported at an incidence of > 2% and at a greater incidence than that in participants treated with placebo are listed in Table 3.

Table 3. Additional Adverse Reactions Reported by ≥ 2% of Children and Adolescents Receiving ORALAIR 300 IR and at a Greater Incidence than that in Participants Treated with Placebo
Adverse Rections | ORALAIR 300 IR (N=154) | PLACEBO (N=158)
Infections and infestations
Tonsillitis | 5.8% | 3.2%
Upper respiratory tract infection | 3.9% | 1.9%
Respiratory, thoracic and mediastinal disorders
Asthma | 7.1% | 3.8%
Dysphonia | 2.6% | 1.3%
Gastrointestinal disorders
Lip pruritus | 3.2% | 0.0%
Skin and subcutaneous tissue disorders
Atopic dermatitis | 3.2% | 0.6%

An open-label study was conducted to evaluate the 30-day safety profile of ORLAIR in 307 children 5 through 9 years of age. Of study participants, 71% were male and 36% had a history of mild intermittent asthma at study entry. Data on race and ethnicity were not systematically captured. Adverse reactions reported at an incidence of > 2% were: throat irritation (22.1%), oral pruritus (11.7%), oral paresthesia (11.1%), tongue pruritus (8.1%), mouth edema (6.2%), cough (6.2%), oropharyngeal pain (4.2%), ear pruritus (5.2%), eye pruritus (4.6%), lip edema (3.3%), vomiting (2.6%), tongue edema (2.3%), abdominal pain (2.3%), oral discomfort (2.3%), and ocular hyperemia (2.0%).

Serious Adverse Reactions

At least 1 serious adverse event was reported in 22 of 1514 (1.5%) pediatric and adult subjects from randomized clinical trials who received ORALAIR at any dose, and 11 of 840 (1.1%) of placebo recipients. Of the 22 serious adverse events in the ORALAIR recipients, 2 were considered "definitely related" to ORALAIR.

The first subject was an adult who experienced a severe hypersensitivity reaction which began 5 minutes after administration of ORALAIR. The symptoms were violent coughing and marked dyspnea. The subject was treated with antihistamines, salbutamol and prednisolone and the reaction resolved without sequelae.

The second subject was an adult who experienced severe laryngeal edema. The subject was treated with prednisolone and event resolved without sequelae.

There was also one case of gastroenteritis with an onset on Day 93 of therapy that was possibly related to ORALAIR.

In the open-label study conducted in 307 children 5 through 9 years of age, 2 serious adverse events were considered "likely" related to ORALAIR.

The first subject was an 8-year-old subject with a history of allergic bronchial asthma who developed oral pruritus, conjunctivitis, urticaria and asthma exacerbation 15 minutes after administration of ORALAIR on Day 5. The subject was treated with antihistamines and inhaled salbutamol and the reactions fully resolved in 30 minutes. The subject continued ORALAIR.

The second subject was a 6-year-old subject who developed severe lip, eye and eyelid swelling after administration of ORALAIR on Day 26 of therapy. The subject was treated with intravenous antihistamines and prednisolone. Reaction fully resolved within 6 hours. Treatment with ORALAIR was discontinued.

6.2 Postmarketing Experience

Post Marketing Safety Studies

A total of 1728 individuals (808 adults; 920 children 5 through 17 years of age) received ORALAIR in post marketing safety studies. Reported adverse reactions included: anaphylactic reaction, oral allergy syndrome, flushing, dyspnea, laryngeal edema, and diarrhea.

Spontaneous Postmarketing Reports

In addition to adverse reactions reported in clinical and post marketing safety studies, the following adverse reactions have been identified during post approval use of ORALAIR. Because these reactions are reported voluntarily from a population of uncertain size, it is not always possible to reliably estimate their frequency or establish a causal relationship to drug exposure: autoimmune thyroiditis, eosinophilic myocarditis, eosinophilic esophagitis, palpitations, tachycardia, hypotension, loss of consciousness, circulatory collapse, malaise, pallor, peripheral vascular disorder, stridor, angioedema, face edema, weight decreased, wheezing, exacerbation of asthma, chest discomfort, oropharyngeal paresthesia, oropharyngeal blistering, headache, dizziness, tinnitus, asthenia, somnolence, anxiety, rash, pruritus, salivary gland enlargement and/or hypersecretion, dry mouth, dry eye, influenza-like syndrome, lymphadenopathy, eosinophil count increased.

8 USE IN SPECIFIC POPULATIONS

8.1 Pregnancy

Risk Summary
All pregnancies have a risk of birth defect, loss, or other adverse outcomes. In the U.S. general population, the estimated background risk of major birth defects and miscarriage in clinically recognized pregnancies is 2-4% and 15-20%, respectively.
Available human data do not establish the presence or absence of ORALAIR-associated risks during pregnancy, labor and delivery.
Two developmental toxicity studies were performed in female rats and female rabbits given doses up to 250 IR/day and 3500 IR/day of ORALAIR, respectively, during gestation.

Data
In developmental toxicity studies, the effect of ORALAIR on embryo/fetal development was evaluated in female rats and female rabbits administered with doses up to 250 IR/day and 3500 IR/day of ORALAIR, respectively, by oral gavage on days 6-17 of gestation for rats, and days 6-18 of gestation for rabbits. The human dose is 300 IR/day. There were no ORALAIR-related fetal malformations or other evidence of teratogenesis noted in these studies.

8.2 Lactation

Risk Summary
Data are not available to assess the effects of ORALAIR on the breastfed child or on milk production/excretion. The developmental and health benefits of breastfeeding should be considered along with the mother’s clinical need for ORALAIR and any potential adverse effects on the breastfed child from ORALAIR or from the underlying maternal condition.

8.4 Pediatric Use

The safety and effectiveness of ORALAIR have not been established in children below 5 years of age.

8.5 Geriatric Use

ORALAIR has not been studied in patients over 65 years of age.

11 DESCRIPTION

ORALAIR (Sweet Vernal, Orchard, Perennial Rye, Timothy, and Kentucky Blue Grass Mixed Pollens Allergen Extract) is a mixed allergen extract of the following five pollens: Sweet Vernal (Anthoxanthum odoratum L), Orchard (Dactylis glomerata L), Perennial Rye (Lolium perenne L), Timothy (Phleum pratense L), and Kentucky Blue Grass (Poa pratensis L).

ORALAIR is available as a sublingual tablet in the following strengths:

- 100 IR (equivalent to approximately 3000 BAU (bioequivalent allergy units)
- 300 IR (equivalent to approximately 9000 BAU

Inactive ingredients: mannitol, microcrystalline cellulose, croscarmellose sodium, colloidal anhydrous silica, magnesium stearate and lactose monohydrate.

12 CLINICAL PHARMACOLOGY

12.1 Mechanism of Action

The precise mechanisms of action of allergen immunotherapy are not known.

13 NONCLINICAL TOXICOLOGY

13.1 Carcinogenesis, Mutagenesis, Impairment of Fertility

No carcinogenicity studies were conducted in animals. There was no evidence of mutagenic or clastogenic activity in response to ORALAIR in the in vitro bacterial mutagenesis assay and mouse lymphoma thymidine kinase cell assay or the in vivo bone marrow micronucleus and unscheduled DNA synthesis tests in rats.

No fertility study was conducted with ORALAIR.

14 CLINICAL STUDIES

The efficacy of ORALAIR for the treatment of grass pollen-induced allergic rhinoconjunctivitis was investigated in five double-blind, placebo-controlled clinical trials: four natural field studies and an environmental exposure chamber study.

The natural field studies included these trials, each conducted over a single season (two in adults and one in adolescents and children) and one five-year study (adults). Participants received ORALAIR or placebo daily for four months prior to grass pollen season and throughout grass pollen season.

Study participants reported at least a two grass pollen season history of rhinoconjunctivitis symptoms. For the European studies, subjects had a positive skin prick test to 5-grass pollen extract and positive in vitro testing for timothy grass-specific serum IgE. For the US study, subjects had a positive skin prick test to Timothy grass pollen extract.

With the exception of those with mild intermittent asthma, patients with asthma were excluded. Approximately 16% had asthma at baseline and 65% were polysensitized (i.e., sensitized to the 5-grass pollen allergen extract and at least one other unrelated allergen). Overall, the mean age of study participants was 28 years and 56% were male.

Natural Field Studies

In the natural field studies, efficacy of ORALAIR as immunotherapy to treat symptoms of allergic rhinoconjunctivitis due to the grass pollens included in ORALAIR was assessed via daily recording of symptoms and rescue medication use. The daily Combined Score (CS, range: 0-3) equally weights symptoms and rescue medication use. The daily Rhinoconjunctivitis Total Symptom Score (RTSS, range 0-18) is the total of the six individual symptom scores (sneezing, rhinorrhea, nasal pruritus, nasal congestion, ocular pruritus and watery eyes) each graded by participants on a 0 (no symptoms) to 3 (severe symptoms) scale. The daily Rescue Medication Score (RMS, range 0-3) grades the intake of rescue medication as 0 = absent, 1 = antihistamine, 2 = nasal corticosteroid, 3 = oral corticosteroid. In case of multiple medications, the higher score is retained. Least Squares (LS) means are within-group means adjusted for the covariates in the statistical models (i.e., analyses of covariance for average scores and linear mixed models with repeated measures for daily scores). The Relative Difference is the LS mean difference between ORALAIR and Placebo divided by the LS mean of Placebo, expressed as a percentage.

US Study

In this study, 473 adults aged 18 through 65 years received ORALAIR or placebo, starting approximately four months prior to the expected onset of the grass-pollen season and continuing for the duration of the pollen season. The results of the analysis of the daily Combined Score (CS), daily Rhinoconjunctivitis Total Symptom Score (RTSS), and daily Rescue Medication Score (RMS) are summarized in Table 4.

Table 4. Daily Combined Score (CS), Daily Rhinoconjunctivitis Total Symptom Score (RTSS), and Daily Rescue Medication Score (RMS) during the Grass Pollen Period (US study)
Efficacy endpoint | ORALAIR; (N=208); LS* Mean | Placebo; (N=228); LS Mean | LS Mean; Difference; ORALAIR; - Placebo | Relative Difference
Efficacy endpoint | ORALAIR; (N=208); LS* Mean | Placebo; (N=228); LS Mean | LS Mean; Difference; ORALAIR; - Placebo | Estimate | 95% CI
Daily CS† | 0.32 | 0.45 | -0.13 | -28.2% | [-43.4%;-13.0%]
Daily RTSS‡ | 3.21 | 4.16 | -0.95 | -22.9% | [-38.2%;-7.5%]
Daily RMS‡ | 0.11 | 0.20 | -0.09 | -46.5% | [-73.9%;-19.2%]

* LS: Least Squares
† Primary efficacy analysis
‡ Secondary efficacy analysis

European Study

In this study, adults aged 18 to 45 years received one of 3 different doses of 5-grass pollen extract sublingual tablet or placebo. A total of 311 subjects received ORALAIR or placebo starting approximately 4 months prior to the expected onset of the grass pollen season and continuing for the duration of the grass pollen season. The results of the analysis of the daily CS, daily RTSS and daily RMS for ORALAIR (300 IR) are shown in Table 5.

Table 5. Daily Combined Score (CS), Daily Rhinoconjunctivitis Total Symptom Score (RTSS), and Daily Rescue Medication Score (RMS) during the Grass Pollen Period (European study)
Efficacy endpoint | ORALAIR (N=136) LS* Mean | Placebo (N=148) LS Mean | LS Mean; Difference; ORALAIR; - Placebo | Relative Difference
Efficacy endpoint | ORALAIR (N=136) LS* Mean | Placebo (N=148) LS Mean | LS Mean; Difference; ORALAIR; - Placebo | Estimate | 95% CI
Daily CS | 0.50 | 0.70 | -0.21 | -29.6% | [-43.1%;-16.1%]
Daily RTSS | 3.48 | 4.91 | -1.44 | -29.2% | [-43.4%;-15.1%]
Daily RMS | 0.41 | 0.59 | -0.18 | -30.1% | [-49.5%;-10.6%]

* LS: Least Squares

Long Term Study

In this study, adults received ORALAIR or placebo according to two different treatment regimens. A total of 426 subjects received ORALAIR or placebo starting approximately 4 months prior to the grass pollen season and continuing for the entire season. Subjects were treated for three consecutive grass pollen seasons (Year 1 to Year 3). The primary evaluation was the Year 3 pollen period. Participants then entered two years of immunotherapy-free follow-up (Year 4 and Year 5). The results of the analysis of the daily Combined Score for ORALAIR (4M) for treatment Years 1-3 are summarized in Table 6. Data are insufficient to demonstrate efficacy for one or two years after discontinuation of ORALAIR.

Table 6. Analysis of Daily Combined Score for Each Grass Pollen Period (Long Term study)
Year | ORALAIR (4M) |  | Placebo |  | LS Mean; Difference; ORALAIR; - Placebo | Relative Difference
Year | N | LS* Mean | N | LS Mean | LS Mean; Difference; ORALAIR; - Placebo | Estimate | 95% CI
Year 1 | 188 | 0.56 | 205 | 0.67 | -0.11 | -16.4% | [-27.0%;-5.8%]
Year 2 | 160 | 0.35 | 172 | 0.56 | -0.21 | -38.0% | [-53.4%;-22.6%]
Year 3 | 149 | 0.31 | 165 | 0.50 | -0.19 | -38.3% | [-54.7%;-22.0%]

* LS: Least Squares

Pediatric Study

In this study, 278 children and adolescents 5 through 17 years of age received ORALAIR or placebo starting approximately 4 months prior to the grass-pollen season and continuing for the duration of the pollen season. The results of the daily CS, daily RTSS, and daily RMS are summarized in Table 7.

Table 7. Daily Combined Score (CS), Daily Rhinoconjunctivitis Total Symptom Score (RTSS), Daily Rescue Medication Score (RMS) during the Grass Pollen Period (Pediatric study)
Efficacy endpoint | ORALAIR (N=131) LS* Mean | Placebo (N=135) LS Mean | LS Mean; Difference; ORALAIR; - Placebo | Relative Difference
Efficacy endpoint | ORALAIR (N=131) LS* Mean | Placebo (N=135) LS Mean | LS Mean; Difference; ORALAIR; - Placebo | Estimate | 95% CI
Daily CS | 0.44 | 0.63 | -0.19 | -30.1% | [-46.9%;-13.2%]
Daily RTSS | 2.52 | 3.63 | -1.11 | -30.6% | [-47.0%;-14.1%]
Daily RMS | 0.46 | 0.65 | -0.19 | -29.5% | [-50.9%;-8.0%]

* LS: Least Squares

Allergen Environmental Chamber Study

In an allergen environmental chamber study, 89 adults with grass pollen-associated allergic rhinoconjunctivitis were challenged with four of the five grass pollens contained in ORALAIR at baseline and after 4 months of treatment with ORALAIR (n=45) or placebo (n=44). The average Rhinoconjunctivitis Total Symptom Score (RTSS) of each group during the 4 hours of the allergen challenge was assessed; use of rescue medication was not permitted. The results of this study are shown in Table 8.

Table 8. Average Rhinoconjunctivitis Total Symptom Score (RTSS) during Grass Pollen Allergen Challenge in an Environmental Exposure Chamber after 4 months of ORALAIR or placebo
Efficacy endpoint | ORALAIR (N=45) LS* Mean | Placebo (N=44) LS Mean | LS Mean; Difference; ORALAIR; - Placebo | Relative Difference
Efficacy endpoint | ORALAIR (N=45) LS* Mean | Placebo (N=44) LS Mean | LS Mean; Difference; ORALAIR; - Placebo | Estimate | 95% CI
Average RTSS† | 4.88 | 6.84 | -1.97 | -28.7% | [-43.7%;-13.7%]

* LS: Least Squares
† Primary efficacy analysis

16 HOW SUPPLIED/STORAGE AND HANDLING

ORALAIR is available as a sublingual tablet equivalent to 100 IR and 300 IR of five grass mixed pollens allergen extract.

 | Description | NDC Number
Children and; Adolescents Sample Kit (5 to 17 years of age) | One box of the 100 IR; Starter Pack Two boxes of the 300 IR; Sample Packs | NDC 59617-0020-1
Adult Sample Kit (18 to 65 years of age) | One box of 300 IR Starter; Pack Two boxes of 300 IR; Sample Packs | NDC 59617-0025-1
Children and; Adolescents Starter Pack (5 to 17 years of age) | 1 blister pack of three 100; IR tablets | NDC 59617-0010-1
Adult Starter Pack (18 to 65 years of age) | 1 blister pack of three 300; IR tablets | NDC 59617-0016-1
Sample Pack | 1 blister pack of three 300; IR tablets | NDC 59617-0015-3
Commercial Pack | 1 blister pack of thirty 300; IR tablets | NDC 59617-0015-2

Storage: Store at controlled room temperature (20°C-25°C/68°F-77°F); excursions permitted to 15-30°C (59-86°F). Protect from moisture.

17 PATIENT COUNSELING INFORMATION

- Advise the patient to read the FDA-approved patient labeling (Medication Guide).
- Keep ORALAIR out of the reach of children.

- Inform patients that ORALAIR is used for sublingual immunotherapy for the treatment of grass pollen-induced allergic rhinitis with or without conjunctivitis and is not indicated for the immediate relief of allergy symptoms.

Severe Allergic Reactions

- Advise patients that ORALAIR may cause systemic allergic reactions, including anaphylactic reactions, and severe local allergic reactions [ See Warnings and Precautions (5.1)].

- Educate patients about the signs and symptoms of a severe systemic allergic reaction and a severe local allergic reaction. The signs and symptoms of a severe allergic reaction may include: syncope, dizziness, hypotension, tachycardia, dyspnea, wheezing, bronchospasm, chest discomfort, cough, abdominal pain, vomiting, diarrhea, rash, pruritus, flushing, and urticaria [ See Warnings and Precautions (5.2)].

- Ensure that patients have injectable epinephrine available and are appropriately trained in its use. Instruct patients who experience a severe allergic reaction to seek immediate medical care, discontinue therapy, and resume treatment only at the instruction of a physician [ See Warnings and Precautions (5.2)].

- Inform the patient that the first dose of ORALAIR is administered in a healthcare setting under the supervision of a physician and s/he will be monitored for at least 30 minutes to watch for signs and symptoms of a severe systemic or a severe local allergic reaction [ See Dosage and Administration (2.2)].

- Inform parents/guardians that ORALAIR should be administered to children only under adult supervision [ See Dosage and Administration (2.2)].

- Because of the risk of eosinophilic esophagitis, instruct patients with severe or persistent symptoms of esophagitis to discontinue ORALAIR and to contact their healthcare professional. [ See Warnings and Precautions (5.3)]

Asthma

- Instruct patients with asthma that if they have difficulty breathing or if asthma becomes difficult to control, they are to stop taking ORALAIR and contact their healthcare professional immediately [ See Warnings AND Precautions (5.3)].

Administration Instructions

- Instruct patients to carefully remove the ORALAIR tablet from the blister just prior to dosing and to take the sublingual tablet immediately by placing it under the tongue where it will dissolve. Also instruct patients to avoid swallowing for about 1 minute, to wash their hands after handling the tablet, and to avoid food or beverages for 5 minutes after taking the tablet [ See Dosage and Administration (2.2)].

ORALAIR® is a registered trademark of Stallergenes SAS

Manufactured by:
Stallergenes SAS
Antony, 92183, France
U.S. License # 1893

Distributed by:
GREER Laboratories, Inc.
Lenoir, N.C. 28645

MEDICATION GUIDE

ORALAIR® (OR-AL-AIR): (Sweet Vernal, Orchard, Perennial Rye, Timothy, and Kentucky Blue Grass Mixed Pollens Allergen Extract)

Carefully read this Medication Guide before you or your child start taking ORALAIR and each time you get a refill. This Medication Guide does not take the place of talking to your doctor about your medical condition or treatment. Talk with your doctor or pharmacist if there is something you do not understand or you want to learn more about ORALAIR.

What is the Most Important Information I Should Know about ORALAIR?

ORALAIR can cause severe allergic reactions that may be life-threatening. Symptoms of allergic reactions to ORALAIR include:

- Trouble breathing
- Throat tightness or swelling
- Trouble swallowing or speaking
- Dizziness or fainting
- Rapid or weak heartbeat
- Severe stomach cramps or pain, vomiting, or diarrhea
- Severe flushing or itching of the skin

If any of these symptoms occur, stop taking ORALAIR and immediately seek medical care.

For home administration of ORALAIR, your doctor should prescribe auto-injectable epinephrine for you to keep at home for treating a severe reaction, should one occur. Your doctor will train and instruct you on the proper use of auto-injectable epinephrine.

What is ORALAIR

ORALAIR is a prescription medicine used for sublingual (under the tongue) immunotherapy prescribed to treat sneezing, runny or itchy nose, nasal congestion or itchy and watery eyes due to allergy to these grass pollens. ORALAIR may be prescribed for persons 5 to 65 years of age whose doctor has confirmed are allergic to any of the grass pollens contained in ORALAIR.

ORALAIR is taken for about four months before the expected start of the grass pollen season and is continued throughout the grass pollen season.

ORALAIR is NOT a medication that gives immediate relief of allergy symptoms.

Who Should Not Take ORALAIR

You or your child should not take ORALAIR if:

- You or your child has severe, unstable, or uncontrolled asthma

- You or your child had a severe allergic reaction in the past that included any of these symptoms:

- Trouble breathing
- Dizziness or fainting
- Rapid or weak heartbeat

- You or your child has ever had difficulty with breathing due to swelling of the throat or upper airway after using any sublingual immunotherapy before.

- You or your child has ever been diagnosed with eosinophilic esophagitis.

- You or your child is allergic to any of the inactive ingredients contained in ORALAIR

- The inactive ingredients contained in ORALAIR are: mannitol, microcrystalline cellulose, croscarmellose sodium, colloidal

anhydrous silica, magnesium stearate and lactose monohydrate

What Should I Tell My Doctor Before Taking ORALAIR

Your doctor may decide that ORALAIR is not the best course of therapy if:

- You or your child has asthma, depending on how severe it is
- You or your child suffers from lung disease such as chronic obstructive pulmonary disease (COPD)
- You or your child suffers from heart disease such as coronary artery disease, an irregular heart rhythm, or you have hypertension that is not well controlled.
- You or your daughter is pregnant, plans to become pregnant during the time you will be taking ORALAIR, or is breast-feeding.
- You or your child is unable or unwilling to administer auto-injectable epinephrine to treat a severe allergic reaction to ORALAIR
- You or your child is taking certain medicines that enhance the likelihood of a severe reaction, or interfere with the treatment of a severe reaction. These medicines include:

- beta blockers and alpha-blockers (prescribed for high blood pressure)
- cardiac glycosides (prescribed for heart failure or problems with heart rhythm)
- diuretics (prescribed for heart conditions and high blood pressure)
- ergot alkaloids (prescribed for migraine headache)
- monoamine oxidase inhibitors or tricyclic antidepressants (prescribed for depression)
- thyroid hormone (prescribed for low thyroid activity);

You should tell your doctor if you or your child is taking or has recently taken any other medicines, including medicines obtained without a prescription and herbal supplements. Keep a list of them and show it to your doctor and pharmacist each time you get a new supply of ORALAIR. Ask your doctor or pharmacist for advice before taking ORALAIR.

Are there any reasons to stop taking ORALAIR?

Stop ORALAIR and contact your doctor if you or your child:

- has any type of a serious allergic reaction
- develops throat tightness or swelling of the tongue or throat that causes trouble speaking, breathing or swallowing after taking ORALAIR
- has trouble breathing or asthma or another breathing condition that gets worse
- experiences dizziness or fainting
- develops rapid or weak heartbeat
- experiences severe stomach cramps or pain, vomiting, or diarrhea
- develops severe flushing or itching of the skin
- has heartburn, difficulty swallowing, pain with swallowing, or chest pain that does not go away or worsens
- has any mouth surgery procedures (such as tooth removal), develops any mouth infections, ulcers or cuts in the mouth or throat

How should I take ORALAIR?

Take ORALAIR exactly as your doctor tells you.

ORALAIR is a prescription medicine that is placed under the tongue.

- Remove the ORALAIR tablet from the blister just prior to dosing.
- Place the ORALAIR tablet immediately under the tongue until complete dissolution for at least 1 minute before swallowing.
- Do not take ORALAIR with food or beverage. Food and beverage should not be taken for the following 5 minutes.
- Wash hands after handling the tablet.

Take the first tablet of ORALAIR in your doctor's office. After taking the first tablet, you or your child will be observed for at least 30 minutes for symptoms of a serious allergic reaction.

- The first dose for children will be one 100 IR tablet.
- The first dose for adults will be one 300 IR tablet.

If you or your child tolerates the first dose of ORALAIR, you or your child will continue daily ORALAIR therapy at home.

- The first dose at home for children is two 100 IR tablets.
- The first dose at home for adults is one 300 IR tablet.
- After the first dose at home, the dose for children and adults is one 300 IR tablet each day.

Children should be given each dose of ORALAIR by an adult who will watch for any symptoms of a serious allergic reaction.

Take ORALAIR as prescribed by your doctor until the end of the treatment course. If you forget to take ORALAIR, do not take a double dose. Take the next dose at your normal scheduled time the next day. If you don't take ORALAIR for more than one day, contact your health provider before restarting.

What are the possible side effects of ORALAIR?

In children and adults, the most commonly reported side effects were itching of the mouth, lips, tongue or throat. These side effects, by themselves, are not dangerous or life-threatening.

ORALAIR can cause severe allergic reactions that may be life-threatening. Symptoms of allergic reactions to ORALAIR include:

- Trouble breathing
- Throat tightness or swelling
- Trouble swallowing or speaking
- Dizziness or fainting
- Rapid or weak heartbeat
- Severe stomach cramps or pain, vomiting, or diarrhea
- Severe flushing or itching of the skin

For additional information on the possible side effects of ORALAIR, talk with your doctor or pharmacist. You may report side effects to the US Food and Drug Administration (FDA) at 1-800-FDA-1088 or www.fda.gov/medwatch.

How should I store ORALAIR?

Keep ORALAIR out of the reach of children.

Throw away any unused ORALAIR after the expiration date which is stated on the carton and blister pack after "EXP."

Store ORALAIR in a dry place at room temperature, 20°C to 25°C (68°F to 77°F), in the original package.

General information about ORALAIR

Medicines are sometimes prescribed for purposes other than those listed in a Medication Guide. Do not use ORALAIR for a condition for which it was not prescribed. Do not give ORALAIR to other people, even if they have the same symptoms. It may harm them.

This Medication Guide summarizes the most important information about ORALAIR. If you would like more information, talk with your doctor. You can ask your doctor or pharmacist for information about ORALAIR that was written for healthcare professionals. For more information go to www.ORALAIR.com or call Greer Laboratories at 1-855-752-5046.

This Medication Guide has been approved by the U.S. Food and Drug Administration.

ORALAIR® is a registered trademark of Stallergenes SAS

Manufactured by:
Stallergenes SAS
Antony, 92183, France
U.S. License # 1893

Distributed by:
GREER Laboratories, Inc.
Lenoir, N.C. 28645

PRINCIPAL DISPLAY PANEL - CHILDREN KIT CARTON

Oralair®

(Sweet Vernal, Orchard,
Perennial Rye, Timothy, and
Kentucky Blue Grass
Mixed Pollens Allergen
Extract)

Tablet For Sublingual Use

For persons 5 to 17 years of age

Manufactured by:
Stallergenes SAS
92183 Antony France
US License # 1893
STALLERGENES

Distributed by:
GREER Laboratories, Inc.
Lenoir, NC 28645
GREER®

1 box of 3 tablets of 100 IR
2 boxes of 3 tablets of 300 IR

NDC 59617-0020-1

Children and Adolescents
Sample Kit

Dispense the enclosed Medication Guide to the patient.

Store at 20-25°C (68-77°F); excursions permitted
to 15-30°C (59-86°F). [See USP Controlled
Room Temperature.] Protect from moisture.
Store in original package.

USUAL DOSE: See accompanying circular.
INACTIVE INGREDIENTS: Mannitol,
Microcrystalline cellulose, Croscarmellose
sodium, Colloidal anhydrous silica,
Magnesium stearate, Lactose monohydrate.
No preservatives.

Keep out of the reach of children

Rx only

Sample – Not for Sale

41000

PRINCIPAL DISPLAY PANEL - ADULT KIT CARTON

Oralair®

(Sweet Vernal, Orchard,
Perennial Rye, Timothy, and
Kentucky Blue Grass
Mixed Pollens Allergen
Extract)
Tablet For Sublingual Use

For persons 18 to 65 years of age

Manufactured by:
Stallergenes SAS
92183 Antony France
US License # 1893
STALLERGENES

Distributed by:
GREER Laboratories, Inc.
Lenoir, NC 28645
GREER®

3 boxes of 3 tablets of 300 IR

NDC 59617-0025-1

Adult
Sample Kit

Dispense the enclosed Medication Guide to the patient.

Store at 20-25°C (68-77°F); excursions permitted
to 15-30°C (59-86°F). [See USP Controlled
Room Temperature.] Protect from moisture.
Store in original package.

USUAL DOSE: See accompanying circular.
INACTIVE INGREDIENTS: Mannitol,
Microcrystalline cellulose, Croscarmellose
sodium, Colloidal anhydrous silica,
Magnesium stearate, Lactose monohydrate.
No preservatives.

Keep out of the reach of children

Rx only

Sample – Not for Sale

41004

PRINCIPAL DISPLAY PANEL - 300 IR 30 TABLET BLISTER PACK BOX

Oralair®

300 IR

(Sweet Vernal, Orchard,
Perennial Rye, Timothy, and
Kentucky Blue Grass
Mixed Pollens Allergen
Extract)
Tablet For Sublingual Use

For Persons 5 to 65 years of age

Manufactured by:
Stallergenes SAS
92183 Antony France
US License # 1893
STALLERGENES

Distributed by:
GREER Laboratories, Inc.
Lenoir, NC 28645
GREER®

1 blister of 30 tablets of 300 IR

NDC 59617-0015-2

Dispense the enclosed Medication Guide
to the patient

Store at 20-25°C (68-77°F); excursions
permitted to 15-30°C (59-86°F).
[See USP Controlled Room Temperature.]
Protect from moisture. Store in original
package.

USUAL DOSE: See accompanying circular.
INACTIVE INGREDIENTS: Mannitol,
Microcrystalline cellulose, Croscarmellose
sodium, Colloidal anhydrous silica,
Magnesium stearate, Lactose monohydrate.
No preservatives.

Keep out of the reach of children

Rx only

PRINCIPAL DISPLAY PANEL - 300 IR 3 TABLET BLISTER PACK BOX

Oralair®
300 IR

(Sweet Vernal, Orchard,
Perennial Rye, Timothy, and
Kentucky Blue Grass
Mixed Pollens Allergen
Extract)
Tablet For Sublingual Use

For Persons 18 to 65 years of age

Manufactured by:
Stallergenes SAS
92183 Antony France
US License # 1893
STALLERGENES

Distributed by:
GREER Laboratories, Inc.
Lenoir, NC 28645
GREER®

1 blister of 3 tablets of 300 IR

NDC 59617-0016-1

Adult
Starter Pack

Dispense the enclosed Medication Guide
to the patient

Store at 20-25°C (68-77°F); excursions
permitted to 15-30°C (59-86°F).
[See USP Controlled Room Temperature.]
Protect from moisture. Store in original
package.

USUAL DOSE: See accompanying circular.
INACTIVE INGREDIENTS: Mannitol,
Microcrystalline cellulose, Croscarmellose
sodium, Colloidal anhydrous silica,
Magnesium stearate, Lactose monohydrate.
No preservatives.

Keep out of the reach of children

Rx only

Sample – Not for Sale

PRINCIPAL DISPLAY PANEL - 100 IR 3 TABLET BLISTER PACK BOX

Oralair®
100 IR

(Sweet Vernal, Orchard,
Perennial Rye, Timothy, and
Kentucky Blue Grass
Mixed Pollens Allergen
Extract)
Tablet For Sublingual Use

For Persons 5 to 17 years of age

Manufactured by:
Stallergenes SAS
92183 Antony France
US License # 1893
STALLERGENES

Distributed by:
GREER Laboratories, Inc.
Lenoir, NC 28645
GREER®

1 blister of 3 tablets of 100 IR

NDC 59617-0010-1

Children and Adolescents
Starter Pack

Dispense the enclosed Medication Guide
to the patient

Store at 20-25°C (68-77°F); excursions
permitted to 15-30°C (59-86°F).
[See USP Controlled Room Temperature.]
Protect from moisture. Store in original
package.

USUAL DOSE: See accompanying circular.
INACTIVE INGREDIENTS: Mannitol,
Microcrystalline cellulose, Croscarmellose
sodium, Colloidal anhydrous silica,
Magnesium stearate, Lactose monohydrate.
No preservatives.

Keep out of the reach of children

Rx only

Sample – Not for Sale